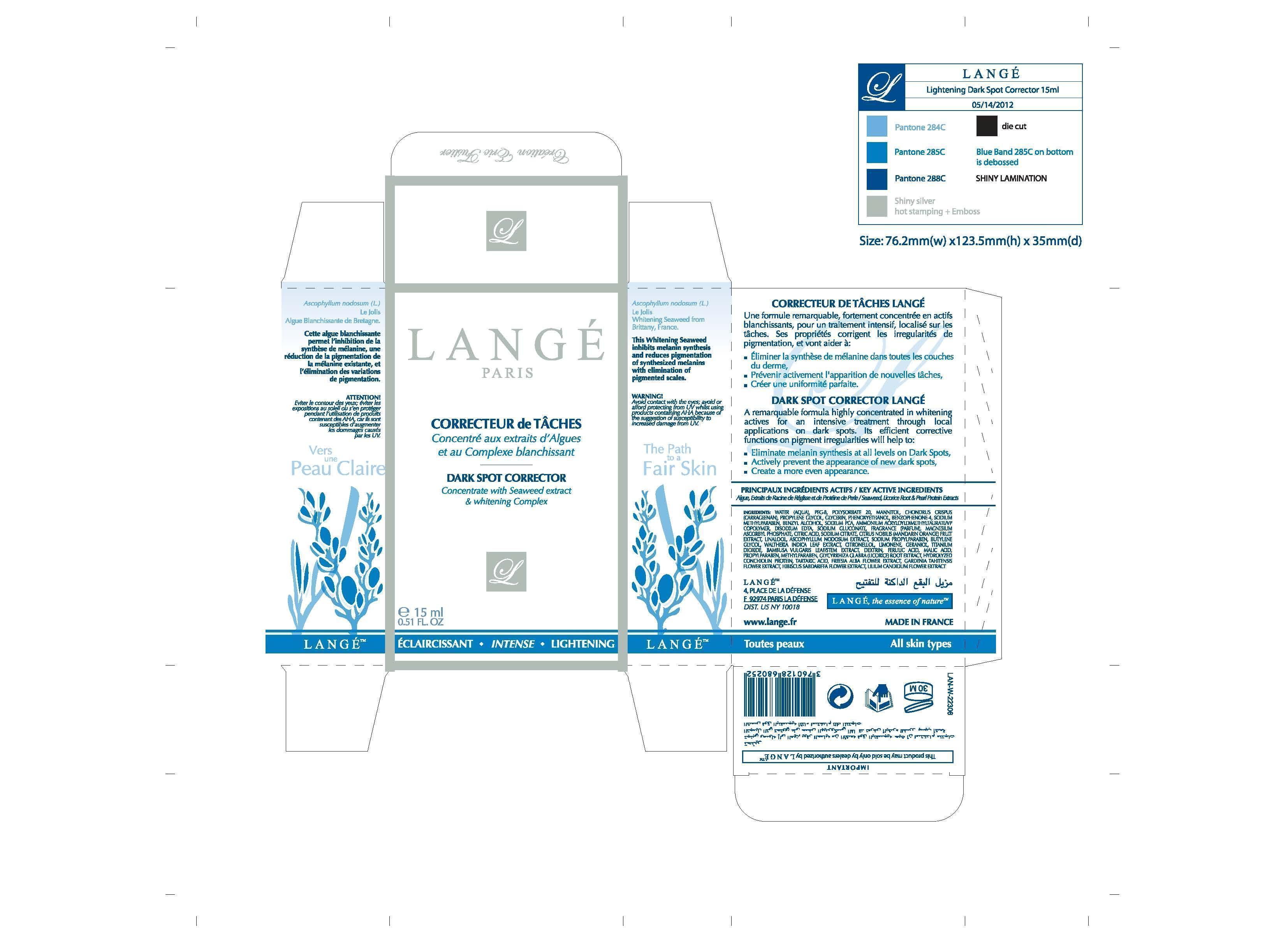 DRUG LABEL: Dark Spot Corrector
NDC: 51830-023 | Form: CREAM
Manufacturer: LANGE SAS
Category: otc | Type: HUMAN OTC DRUG LABEL
Date: 20120718

ACTIVE INGREDIENTS: POLYETHYLENE GLYCOL 400 .3 mg/15 mg
INACTIVE INGREDIENTS: WATER; ASCOPHYLLUM NODOSUM; POLYSORBATE 20; MANNITOL; CHONDRUS CRISPUS; PROPYLENE GLYCOL; GLYCERIN; PHENOXYETHANOL; SULISOBENZONE; METHYLPARABEN SODIUM; BENZYL ALCOHOL; SODIUM PYRROLIDONE CARBOXYLATE; AMMONIUM ACRYLOYLDIMETHYLTAURATE; EDETATE DISODIUM; SODIUM GLUCONATE; MAGNESIUM ASCORBYL PHOSPHATE; CITRIC ACID MONOHYDRATE; SODIUM CITRATE; TANGERINE; ASCOPHYLLUM NODOSUM; PROPYLPARABEN SODIUM; BUTYLENE GLYCOL; WALTHERIA INDICA LEAF; TITANIUM DIOXIDE; BAMBUSA VULGARIS LEAF; ICODEXTRIN; FERULIC ACID; METHYLPARABEN; GLYCYRRHIZA GLABRA; MALIC ACID; PROPYLPARABEN; TARTARIC ACID; FREESIA ALBA FLOWER; GARDENIA TAITENSIS FLOWER; HIBISCUS SABDARIFFA FLOWER; LILIUM CANDIDUM FLOWER

ACTIVE INGREDIENT

Key Active Ingredients Seaweed, Licorice Root Pearl Protein Extracts

PURPOSE

Dark Spot Corrector Lange
A remarquable formula highly concentrated in whitening actives for an intensive treatment through local applications on dark spots. Its efficient corrective functions on pigment irregularities will help to:

- Eliminate melanin synthesis at all levels on Dark Sports,
- Actively prevent the appearance of new dark spots,
- Create a more even appearance.

Keep Out of Reach of Children.

INDICATIONS AND USAGE

This Whitening Seaweed inhibits melanine synthesis and reduces pigmentation of synthesized melanins with elimination of pigmented scales.

WARNING!
Avoid contact with the eyes; avoid or afford protecting UV whilst using products containing AHA because of the suggestion of susceptibility to increased damage from UV.

DOSAGE AND ADMINISTRATION

15ML. 051 FL OZ.

INACTIVE INGREDIENT

WATER, PEG-8, POLYSORBATE 20, MANNITOL, CHONDRUS CRISPUS (CARRAGEENAN) PLANTS AND PLANT EXTRACTS, PROPYLENE GLYCOL, GLYCERIN DENATURANT, PHENOXYETHANOL, BENZOPHENONE-4, SODIUM METHYLPARABEN, BENZYL ALCOHOL PRESERVATIVE, SODIUM PCA, AMMONIUM ACRYLOYLDIMETHYLTAURATE, DISODIUM EDTA CHELATING, SODIUM GLUCONATE CHELATING, MAGNESIUM ASCORBYL PHOSPHATE, CITRIC ACID, SODIUM CITRATE, CITRUS NOBILIS (MANDARIN ORANGE) FRUIT EXTRACT, ASCOPHYLLUM NODOSUM EXTRACT, SODIUM PROPYLPARABEN, BUTYLENE GLYCOL HUMECTANT, WALTHERIA INDICA LEAF EXTRACT,TITANIUM DIOXIDE, BAMBUSA VULGARIS LEAF, DEXTRIN ABSORBENT, FERULIC ACID, METHYLPARABEN PRESERVATIVE, GLYCYRRHIZA GLABRA (LICORICE) ROOT EXTRACT, MALIC ACID, PROPYLPARABEN, HYDROLYZED CONCHIOLIN PROTEIN, TARTARIC ACID, FREESIA ALBA FLOWER EXTRACT, GARDENIA TAHITENSIS FLOWER EXTRACT, HIBISCUS SABDARIFFA FLOWER EXTRACT, LILIUM CANDIDUM FLOWER EXTRACT

PACKAGE LABEL

LANGE PARIS
Dark Spot Corrector
Concentrate with Seaweed extract and whitening complex